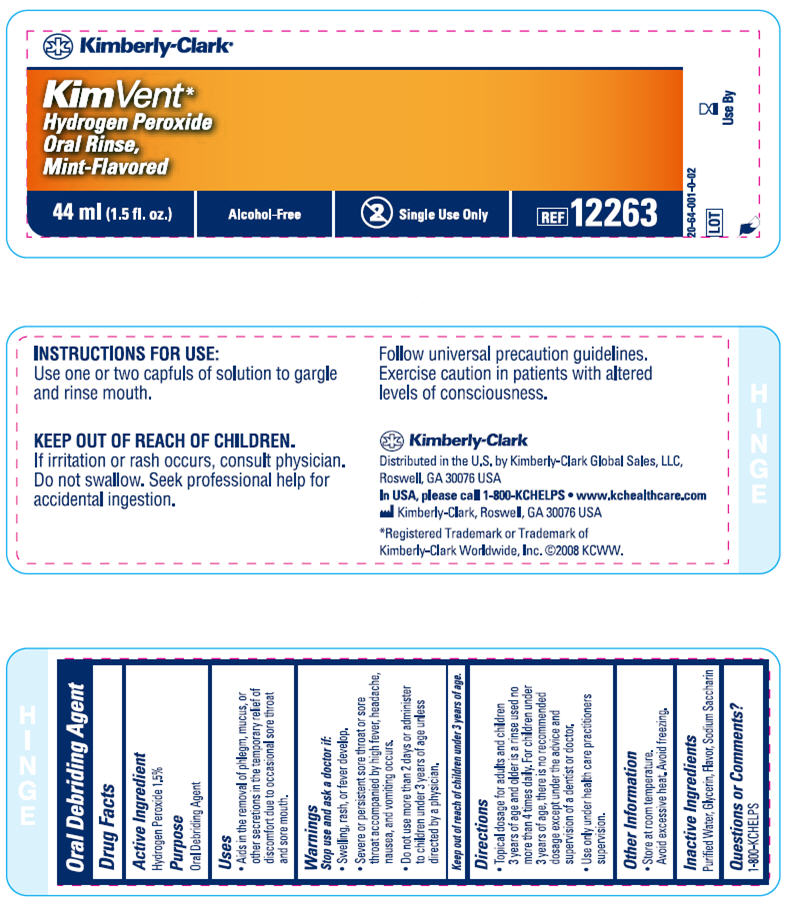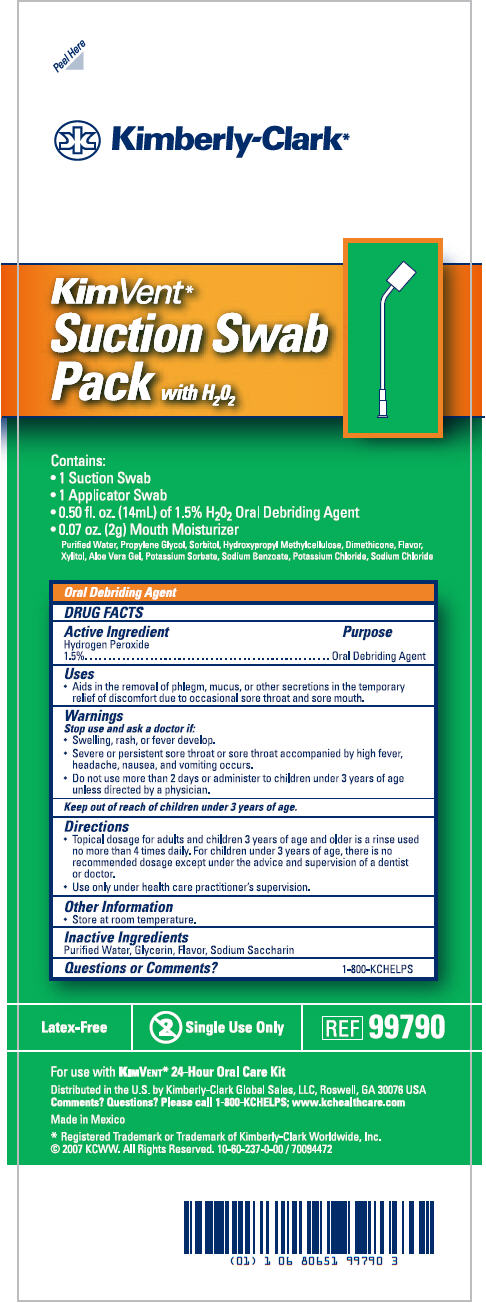 DRUG LABEL: Hydrogen Peroxide
NDC: 69697-990 | Form: LIQUID
Manufacturer: Halyard Health
Category: otc | Type: HUMAN OTC DRUG LABEL
Date: 20150323

ACTIVE INGREDIENTS: Hydrogen Peroxide 0.015 mg/1 mL
INACTIVE INGREDIENTS: Water; Glycerin; Mint; Saccharin Sodium

Hydrogen Peroxide

Oral Debriding Agent

Drug Facts

Active Ingredient

Hydrogen Peroxide 1.5%

Purpose

Oral Debriding Agent

Uses

- Aids in the removal of phlegm, mucus, or other secretions in the temporary relief of discomfort due to occasional sore throat and sore mouth.

Warnings

Stop use and ask a doctor if:

- Swelling, rash, or fever develop.
- Severe or persistent sore throat or sore throat accompanied by high fever, headache, nausea, and vomiting occurs.
- Do not use more than 2 days or administer to children under 3 years of age unless directed by a physician.

Keep out of reach of children under 3 years of age.

Directions

- Topical dosage for adults and children 3 years of age and older is a rinse used no more than 4 times daily. For children under 3 years of age, there is no recommended dosage except under the advice and supervision of a dentist or doctor.
- Use only under health care practitioners supervision.

Other Information

- Store at room temperature.

Inactive Ingredients

Purified Water, Glycerin, Flavor, Sodium Saccharin

Questions or Comments?

1-800-KCHELPS

PRINCIPAL DISPLAY PANEL - 44 ml Bottle Label

Kimberly-Clark*

KimVent*
Hydrogen Peroxide
Oral Rinse,
Mint-Flavored

44 ml (1.5 fl. oz.)

Alcohol-Free

Single Use Only

REF 12263

20-64-001-0-02

LOT

Use By

PRINCIPAL DISPLAY PANEL - Kit Carton

Peel Here

Kimberly-Clark*

KimVent*
Suction Swab
Pack with H2O2

Contains:

- 1 Suction Swab
- 1 Applicator Swab
- 0.50 fl. oz. (14mL) of 1.5% H2O2 Oral Debriding Agent
- 0.07 oz. (2g) Mouth Moisturizer
  Purified Water, Propylene Glycol, Sorbitol, Hydroxypropyl Methylcellulose, Dimethicone, Flavor,
  Xylitol, Aloe Vera Gel, Potassium Sorbate, Sodium Benzoate, Potassium Chloride, Sodium Chloride